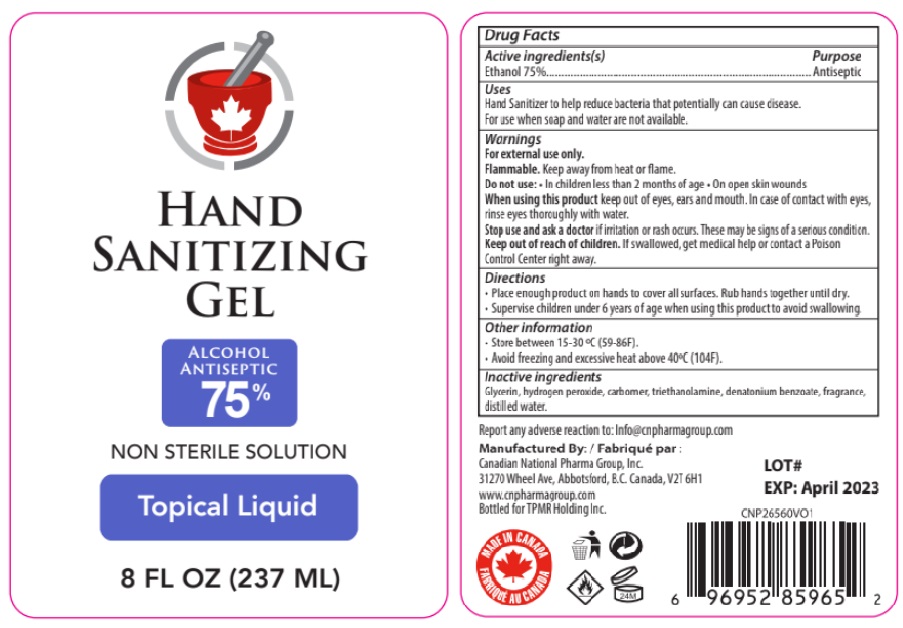 DRUG LABEL: Hand Sanitizing Gel by CN Pharma
NDC: 77536-001 | Form: GEL
Manufacturer: Canadian National Pharma Group Inc
Category: otc | Type: HUMAN OTC DRUG LABEL
Date: 20200918

ACTIVE INGREDIENTS: ALCOHOL 75 mL/100 mL
INACTIVE INGREDIENTS: GLYCERIN; HYDROGEN PEROXIDE; CARBOMER HOMOPOLYMER, UNSPECIFIED TYPE; TROLAMINE; DENATONIUM BENZOATE; WATER; MENTHA SPICATA OIL; EAST INDIAN LEMONGRASS OIL; LAVENDER OIL; TEA TREE OIL; EUCALYPTUS OIL; COCONUT OIL; ORANGE OIL; ALOE; .ALPHA.-TOCOPHEROL

Active Ingredient

Ethanol 75%

Purpose

Antiseptic

Uses

- Hand Sanitizer to help reduce bacteria that potentially can cause disease.
- For use when soap and water are not available.

WARNINGS

For external use only.
Flammable. Keep away from heat or Flame.
Do not use:

- In children less than 2 months of age
- On open skin wounds

When using this product keep out of eyes, ears and mouth. In case of contact with eyes, rinse eyes thoroughly with water.

Stop use and ask a doctor if irritation or rash occurs. These may be signs of a serious condition.

Keep out of reach of children. If swallowed, get medical help or contact a Poison Control Center right away.

Directions

- Place enough product on hands to cover all surfaces. Rub hands together until dry.
- Supervise children under 6 years of age when using this product to avoid swallowing.

Other information

Store between 15-30oC (59-86oF)
Avoid freezing and excessive heat above 40oC (104oF)

Inactive ingredients

Glycerin, hydrogen peroxide, carbomer, triethanolamine, denatonium benzoate, fragrance, distilled water.